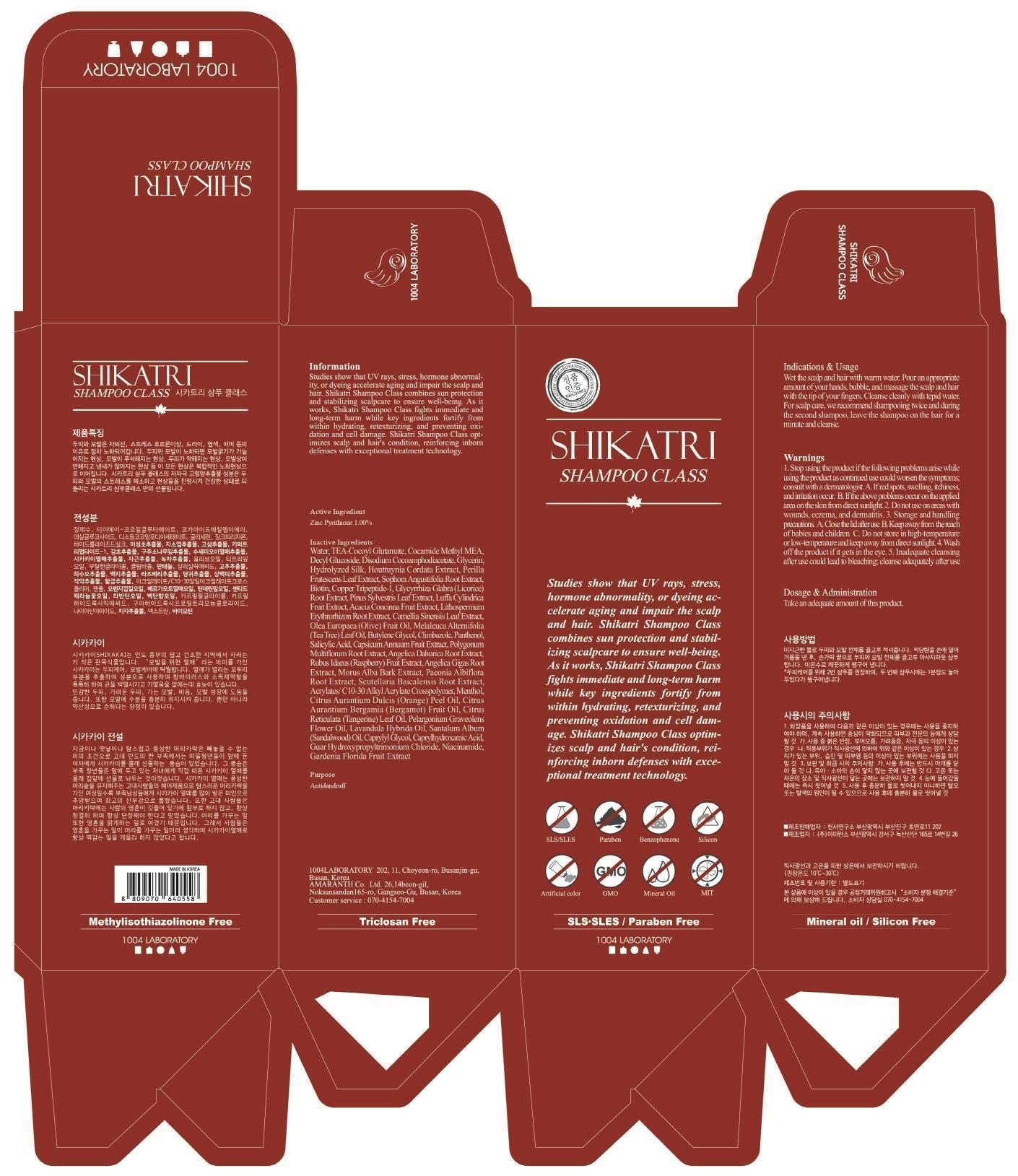 DRUG LABEL: SHIKATRI CLASS
NDC: 69739-010 | Form: SHAMPOO
Manufacturer: 1004LABORATORY
Category: otc | Type: HUMAN OTC DRUG LABEL
Date: 20150424

ACTIVE INGREDIENTS: Pyrithione zinc 3 mg/300 mL
INACTIVE INGREDIENTS: Water; Glycerin

ACTIVE INGREDIENT

Active Ingredient: Zinc Pyrithione 1.00%

INACTIVE INGREDIENT

Inactive Ingredients: Water, TEA-Cocoyl Glutamate, Cocamide Methyl MEA, Decyl Glucoside, Disodium Cocoamphodiacetate, Glycerin, Hydrolyzed Silk, Houttuynia Cordata Extract, Perilla Frutescens Leaf Extract, Sophora Angustifolia Root Extract, Biotin, Copper Tripeptide-1, Glycyrrhiza Glabra (Licorice) Root Extract, Pinus Sylvestris Leaf Extract, Luffa Cylindrica Fruit Extract, Acacia Concinna Fruit Extract, Lithospermum Erythrorhizon Root Extract, Camellia Sinensis Leaf Extract, Olea Europaea (Olive) Fruit Oil, Melaleuca Alternifolia (Tea Tree) Leaf Oil, Butylene Glycol, Climbazole, Panthenol, Salicylic Acid, Capsicum Annuum Fruit Extract, Polygonum Multiflorum Root Extract, Angelica Dahurica Root Extract, Rubus Idaeus (Raspberry) Fruit Extract, Angelica Gigas Root Extract, Morus Alba Bark Extract, Paeonia Albiflora Root Extract, Scutellaria Baicalensis Root Extract, Acrylates/ C10-30 Alkyl Acrylate Crosspolymer, Menthol, Citrus Aurantium Dulcis (Orange) Peel Oil, Citrus Aurantium Bergamia (Bergamot) Fruit Oil, Citrus Reticulata (Tangerine) Leaf Oil, Pelargonium Graveolens Flower Oil, Lavandula Hybrida Oil, Santalum Album (Sandalwood) Oil, Caprylyl Glycol, Caprylhydroxamic Acid, Guar Hydroxypropyltrimonium Chloride, Niacinamide, Gardenia Florida Fruit Extract

PURPOSE

Purpose: Antidandruff

WARNINGS

Warnings: 1. Stop using the product if the following problems arise while using the product as continued use could worsen the symptoms; consult with a dermatologist. A. If red spots, swelling, itchiness, and irritation occur. B. If the above problems occur on the applied area on the skin from direct sunlight 2. Do not use on areas with wounds, eczema, and dermatitis. 3. Storage and handling precautions A. Close the lid after use B. Keep away from the reach of babies and children C. Do not store in high-temperature or low-temperature and keep away from direct sunlight 4. Wash off the product if it gets in the eye 5. Inadequate cleansing after use could lead to bleaching; cleanse adequately after use

KEEP OUT OF REACH OF CHILDREN

Keep away from the reach of babies and children

INDICATIONS & USAGE

Indications & Usage: Wet the scalp and hair with warm water. Pour an appropriate amount of your hands, bubble, and massage the scalp and hair with the tip of your fingers. Cleanse cleanly with tepid water. For scalp care, we recommend shampooing twice and during the second shampoo, leave the shampoo on the hair for a minute and cleanse.

DOSAGE & ADMINISTRATION

Dosage & Administration: Take an adequate amount of this product.